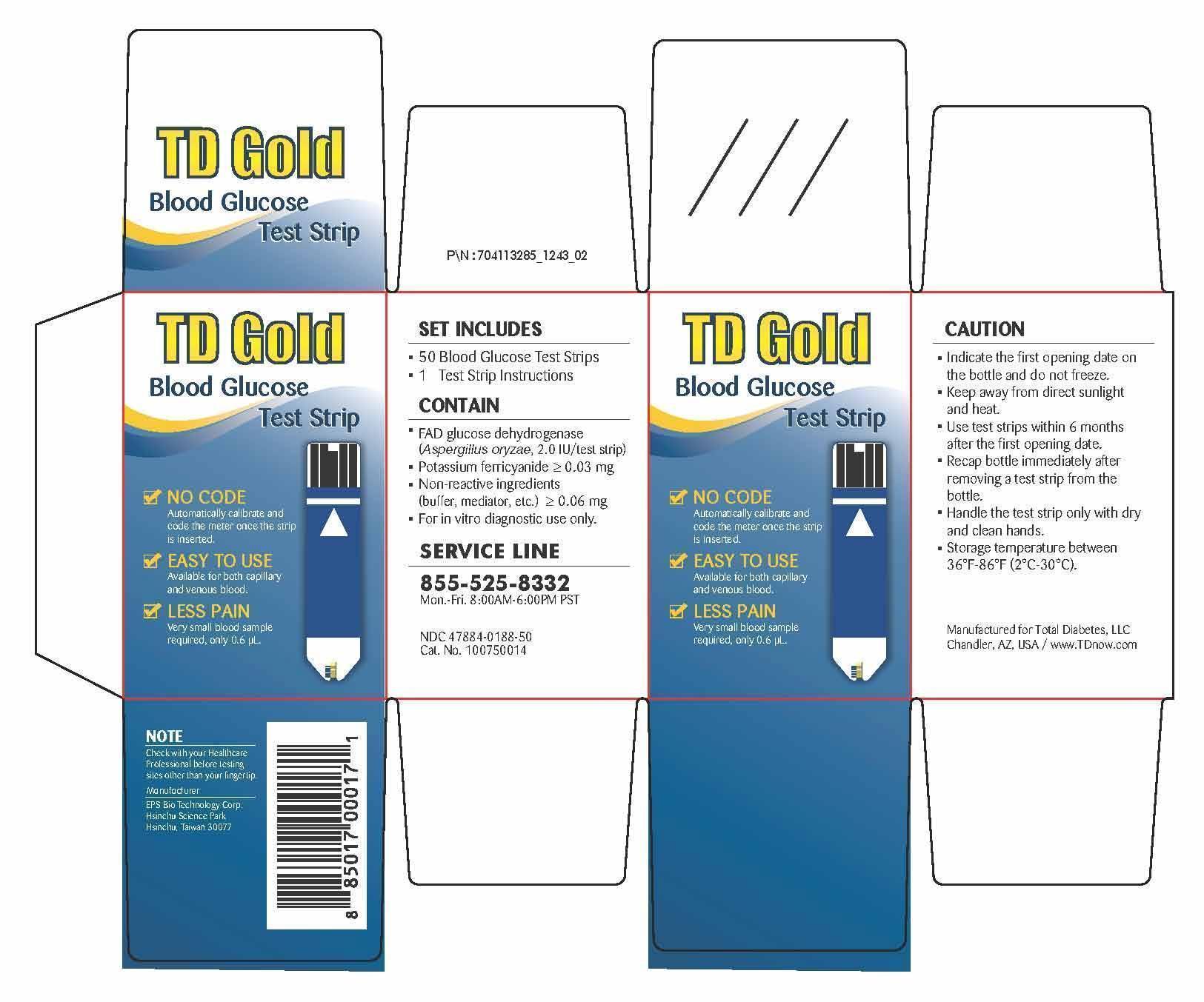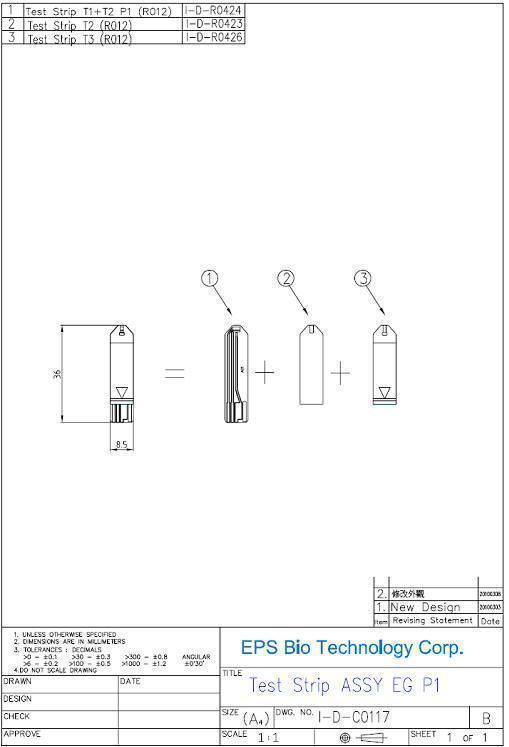 DRUG LABEL: 50 TD Gold Blood Glucose Test Strip
NDC: 47884-188
Manufacturer: EPS Bio Technology Corp
Category: other | Type: MEDICAL DEVICE
Date: 20131022

Home Use Medical Device - TD Gold Blood Glucose test strip